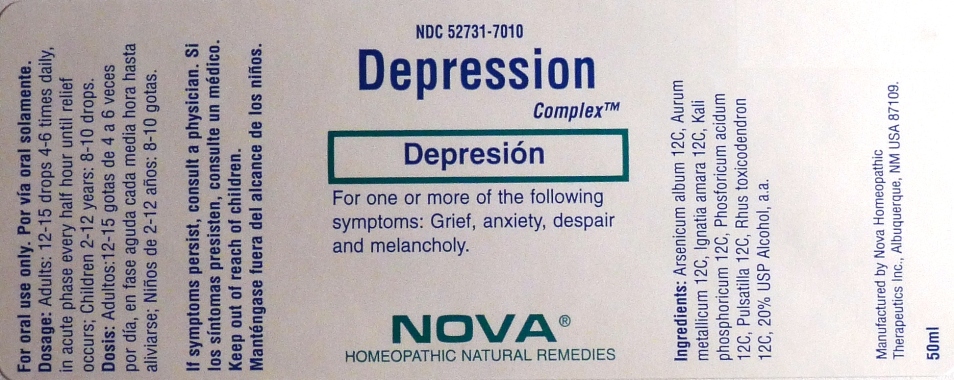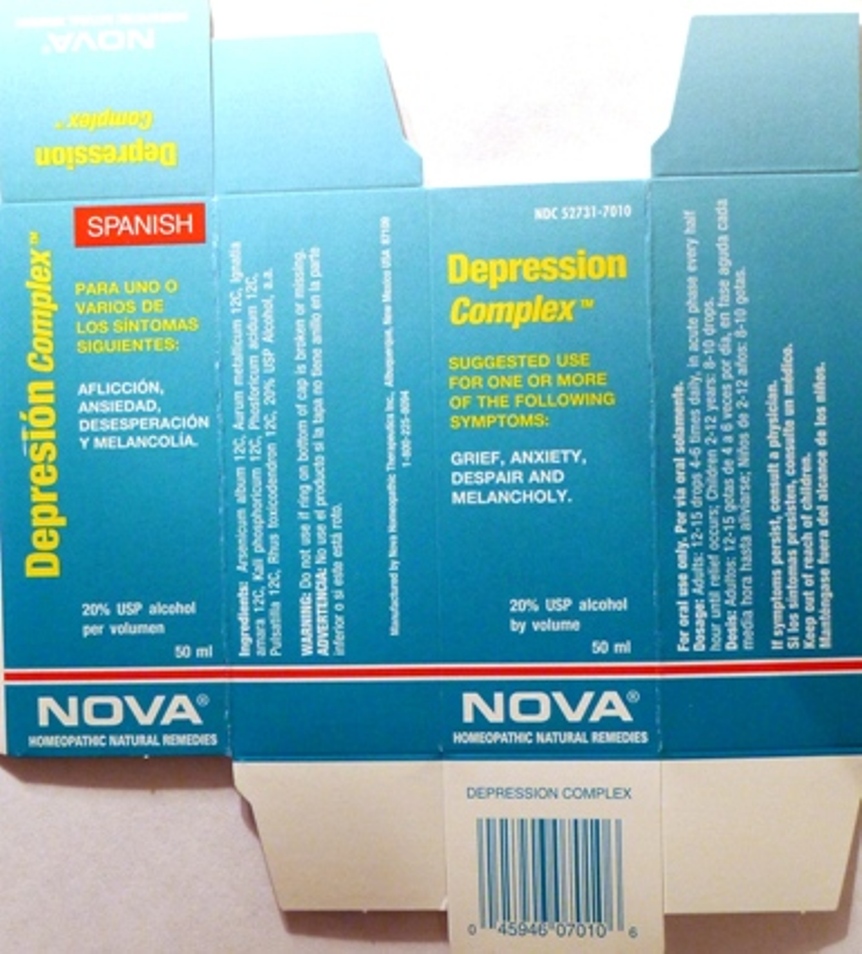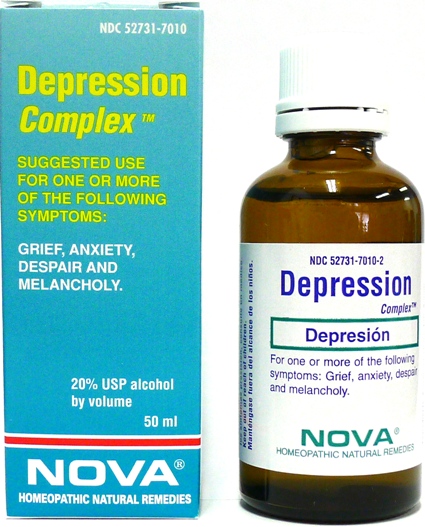 DRUG LABEL: Depression Complex
NDC: 52731-7010 | Form: LIQUID
Manufacturer: Nova Homeopathic Therapeutics, Inc.
Category: homeopathic | Type: HUMAN OTC DRUG LABEL
Date: 20110601

ACTIVE INGREDIENTS: ARSENIC TRIOXIDE 12 [hp_C]/1 mL; GOLD 12 [hp_C]/1 mL; STRYCHNOS IGNATII SEED 12 [hp_C]/1 mL; POTASSIUM PHOSPHATE, DIBASIC 12 [hp_C]/1 mL; PHOSPHORIC ACID 12 [hp_C]/1 mL; PULSATILLA VULGARIS 12 [hp_C]/1 mL; TOXICODENDRON PUBESCENS LEAF 12 [hp_C]/1 mL
INACTIVE INGREDIENTS: ALCOHOL

Depression Complex

PURPOSE

Suggested use for one or more of the following symptoms:

Grief, anxiety, despair and melancholy.

Usage and Dosage:

For oral use only.

DOSAGE AND ADMINISTRATION

Adults:
In Acute Phase:
12-15 drops, every half hour until relief occurs
When Relief Occurs:
12-15 drops, 4-6 times per day
Children 2-12 years:
8-10 drops, 4-6 times per day

Warnings:

Keep out of reach of children.

WARNINGS

If symptoms persist, consult a physician.
Do not use if ring on bottom of cap is broken or missing.

Active Ingredients:

Arsenicum album 12C, Aurum metallicum 12C, Ignatia amara 12C, Kali phosphoricum 12C, Phosforicum acidum 12C, Pulsatilla 12C, Rhus toxicodendron 12C

Inactive Ingredients:

Alcohol, 20% USP

QUESTIONS

Manufactured by Nova Homeopathic Therapeutics Inc., Albuquerque, New Mexico USA 87109
1-800-225-8094

PACKAGE LABEL

Depression Complex Product

Depression Complex Bottle Label

Depression Complex Box